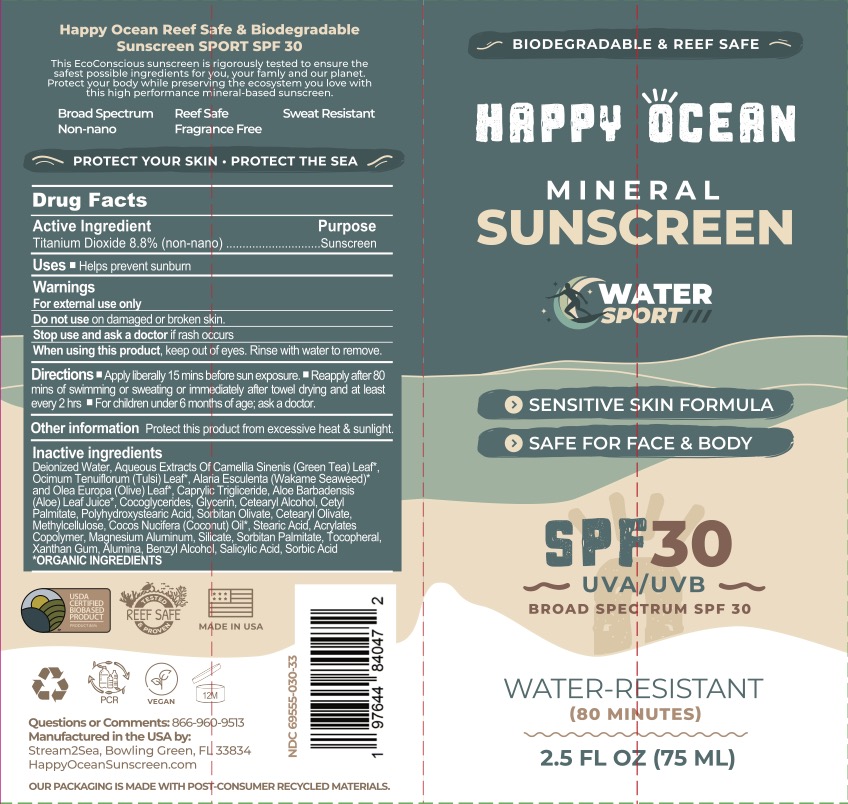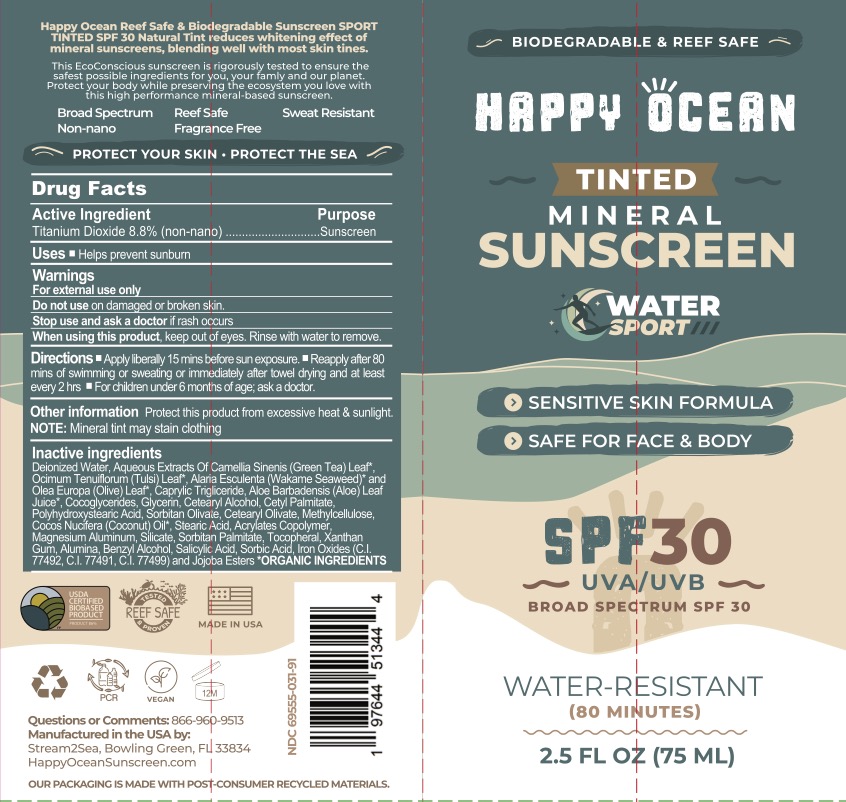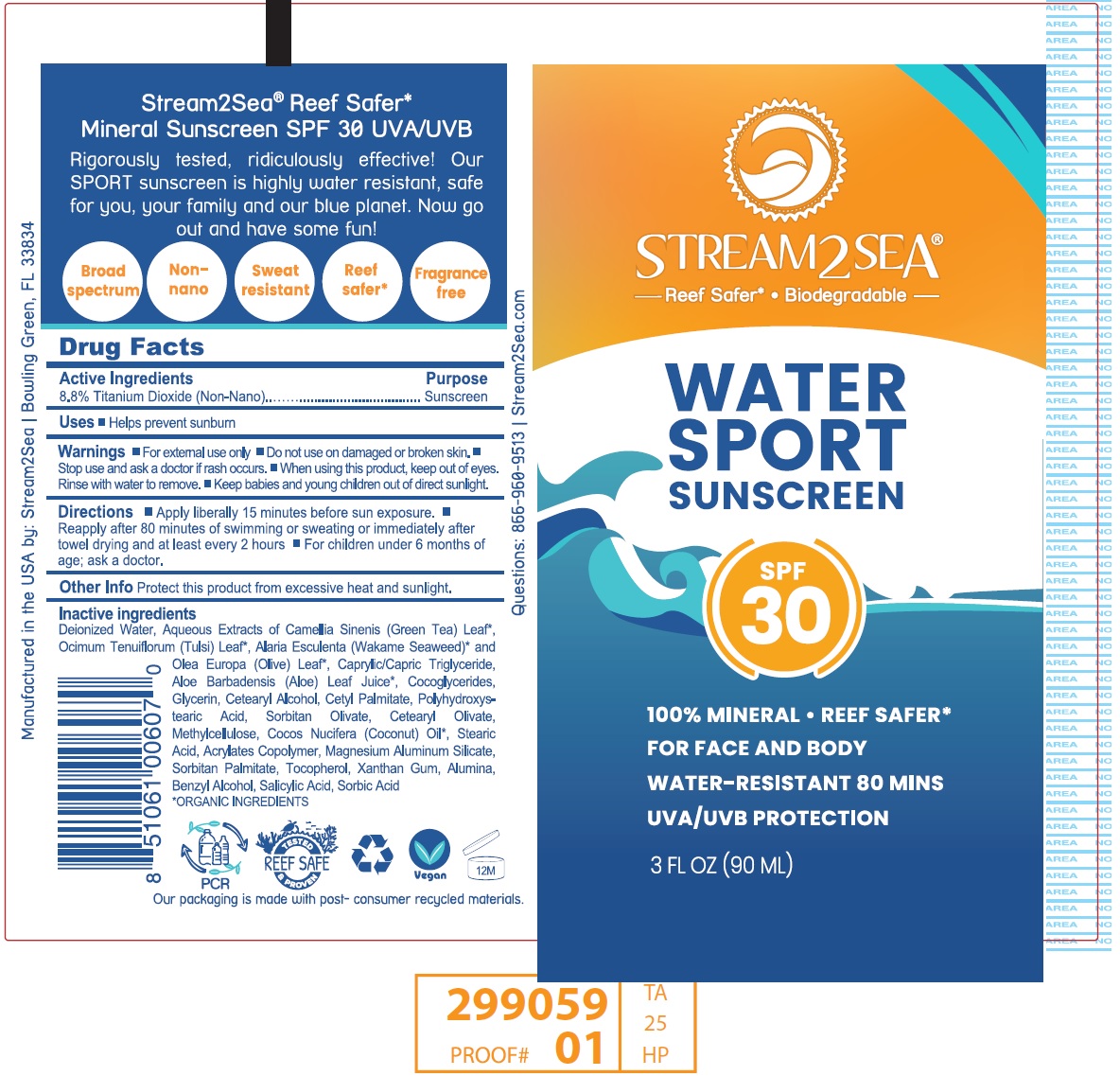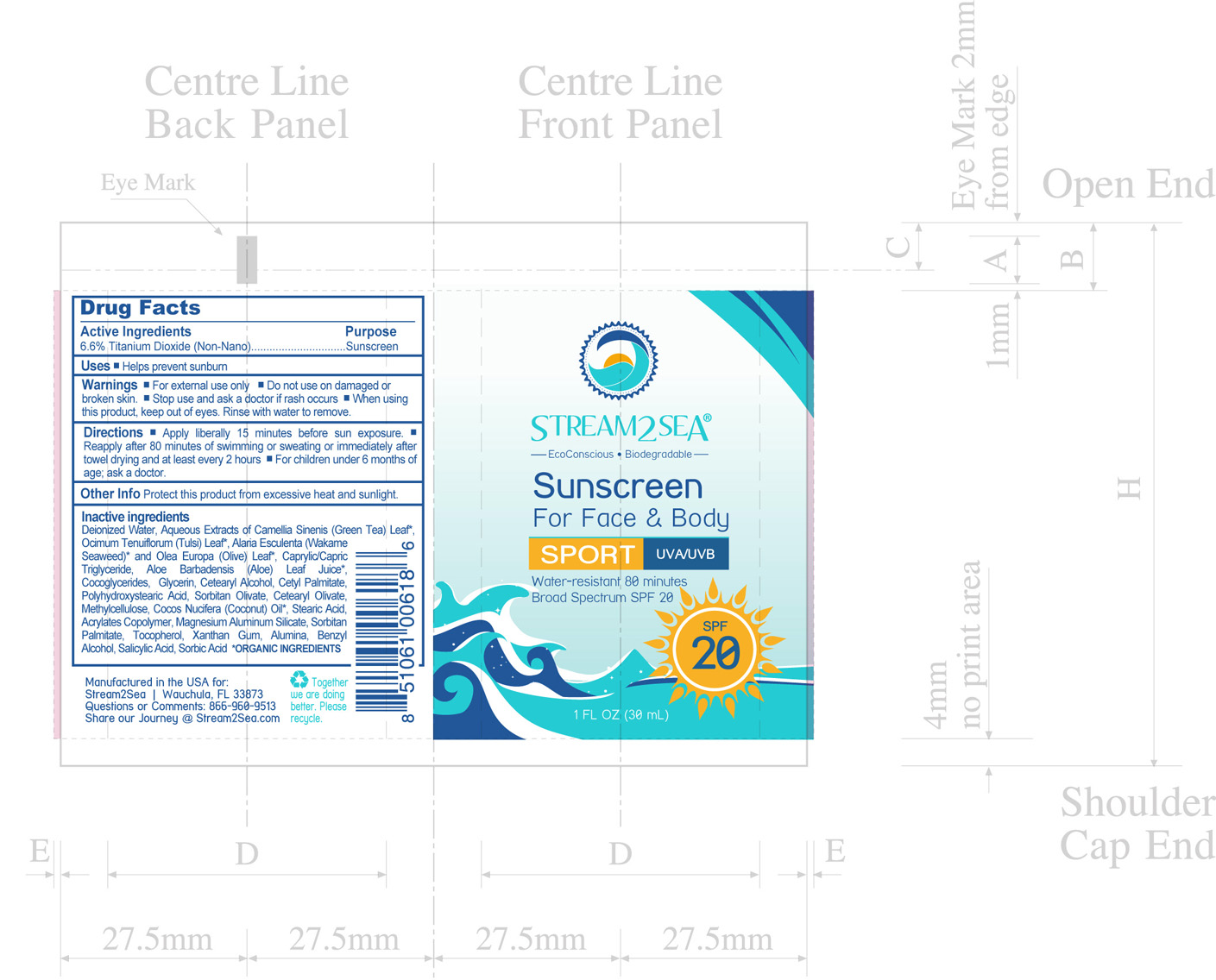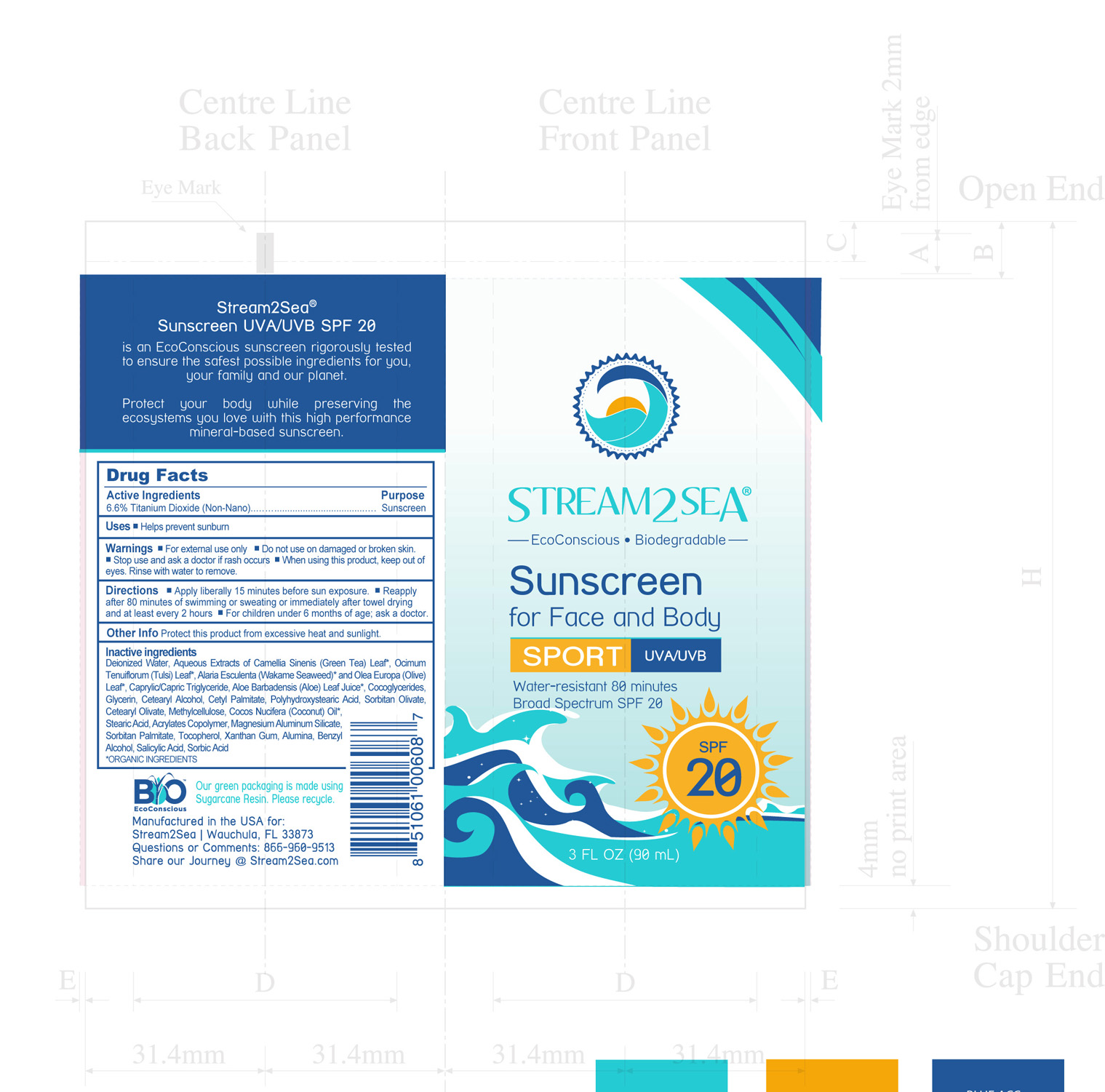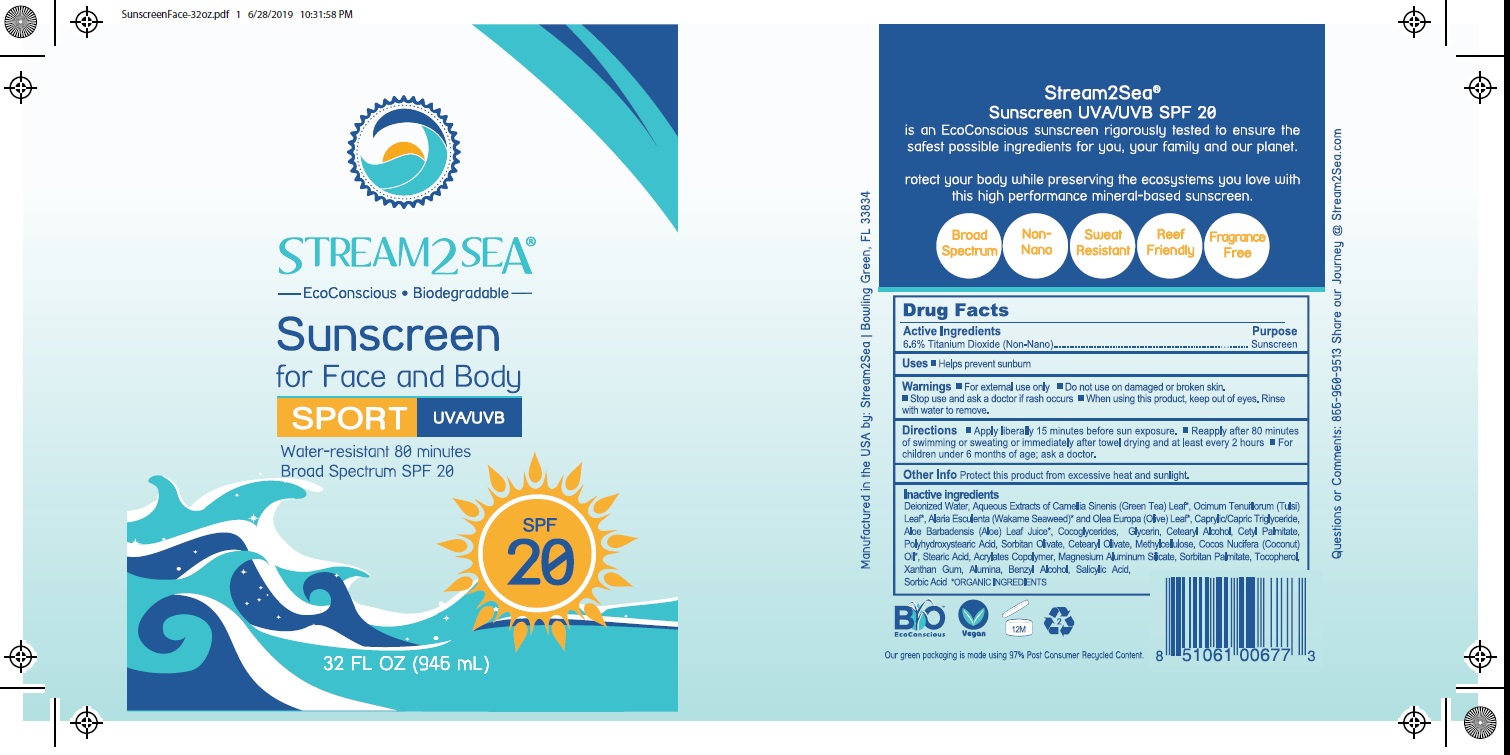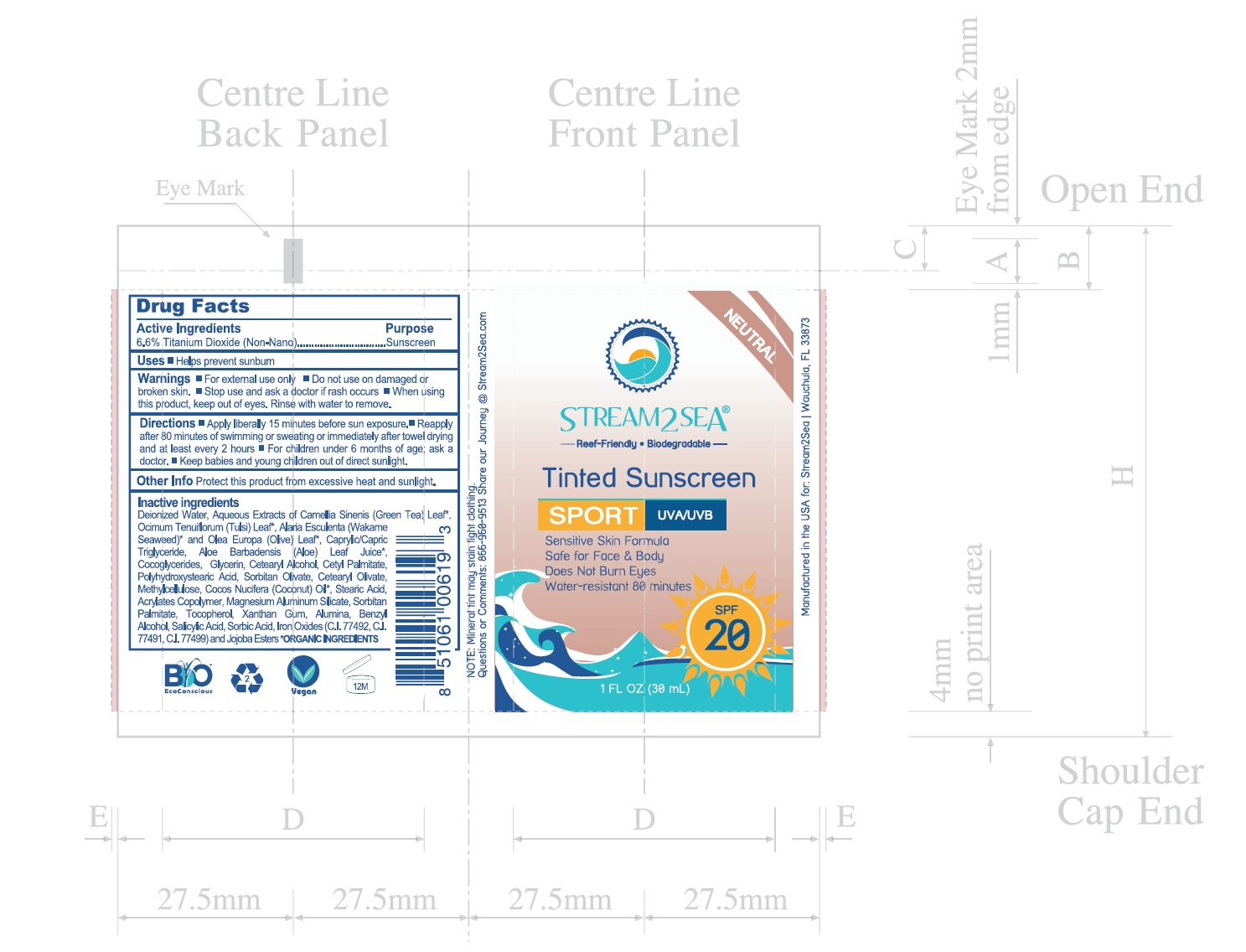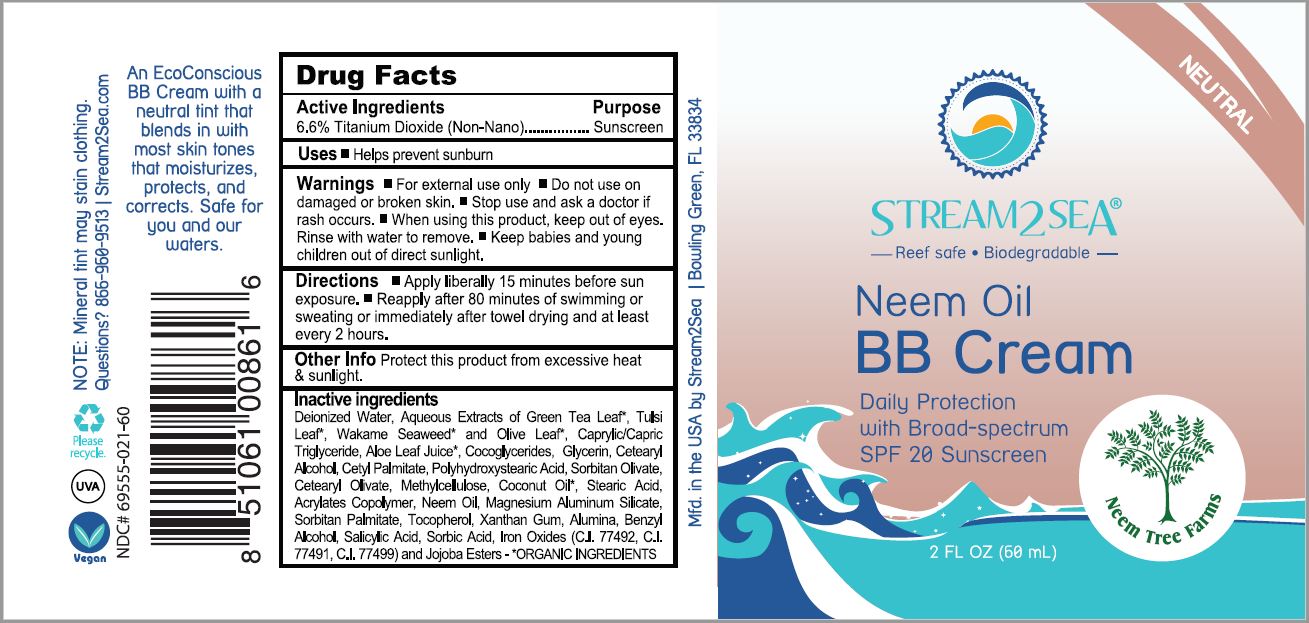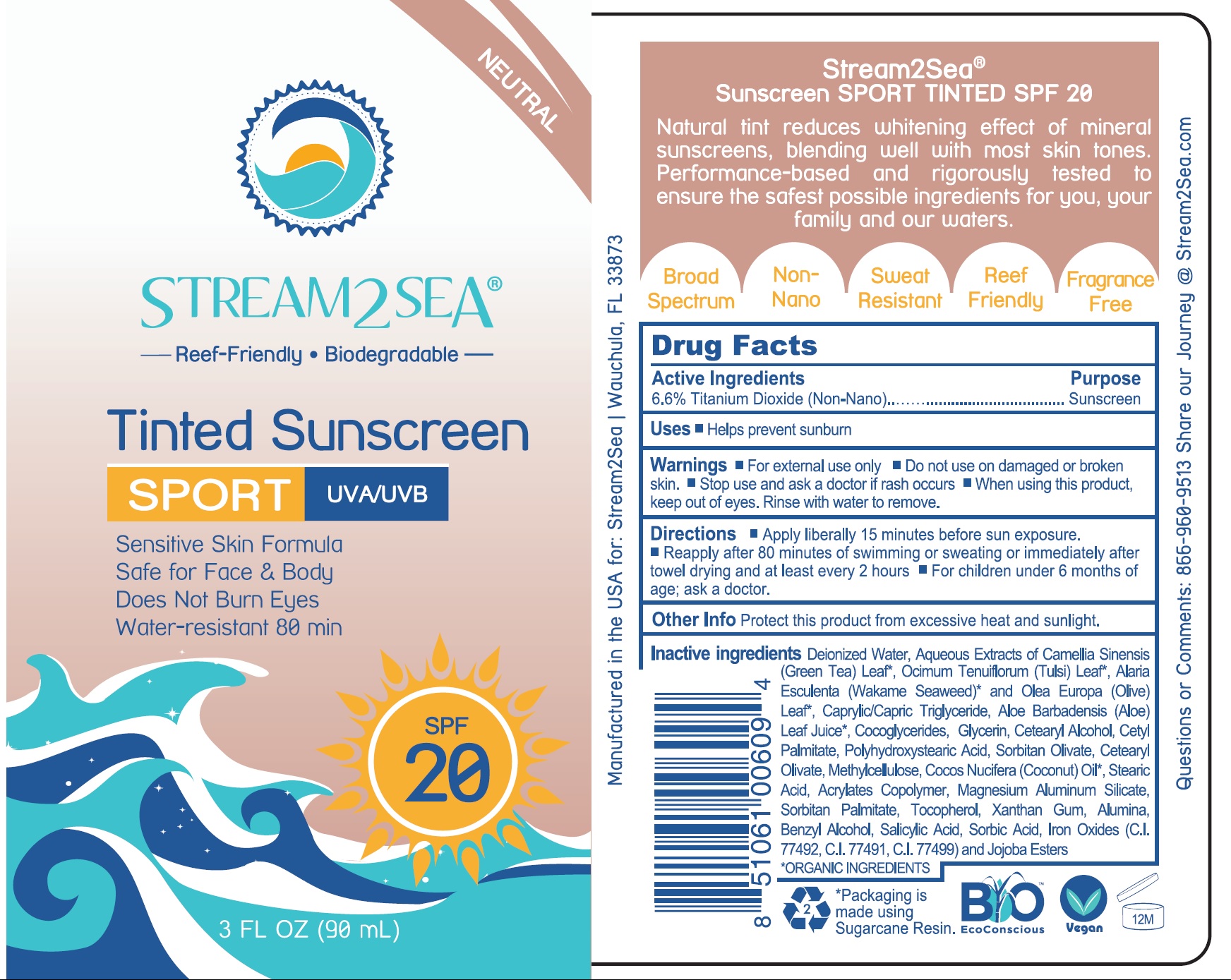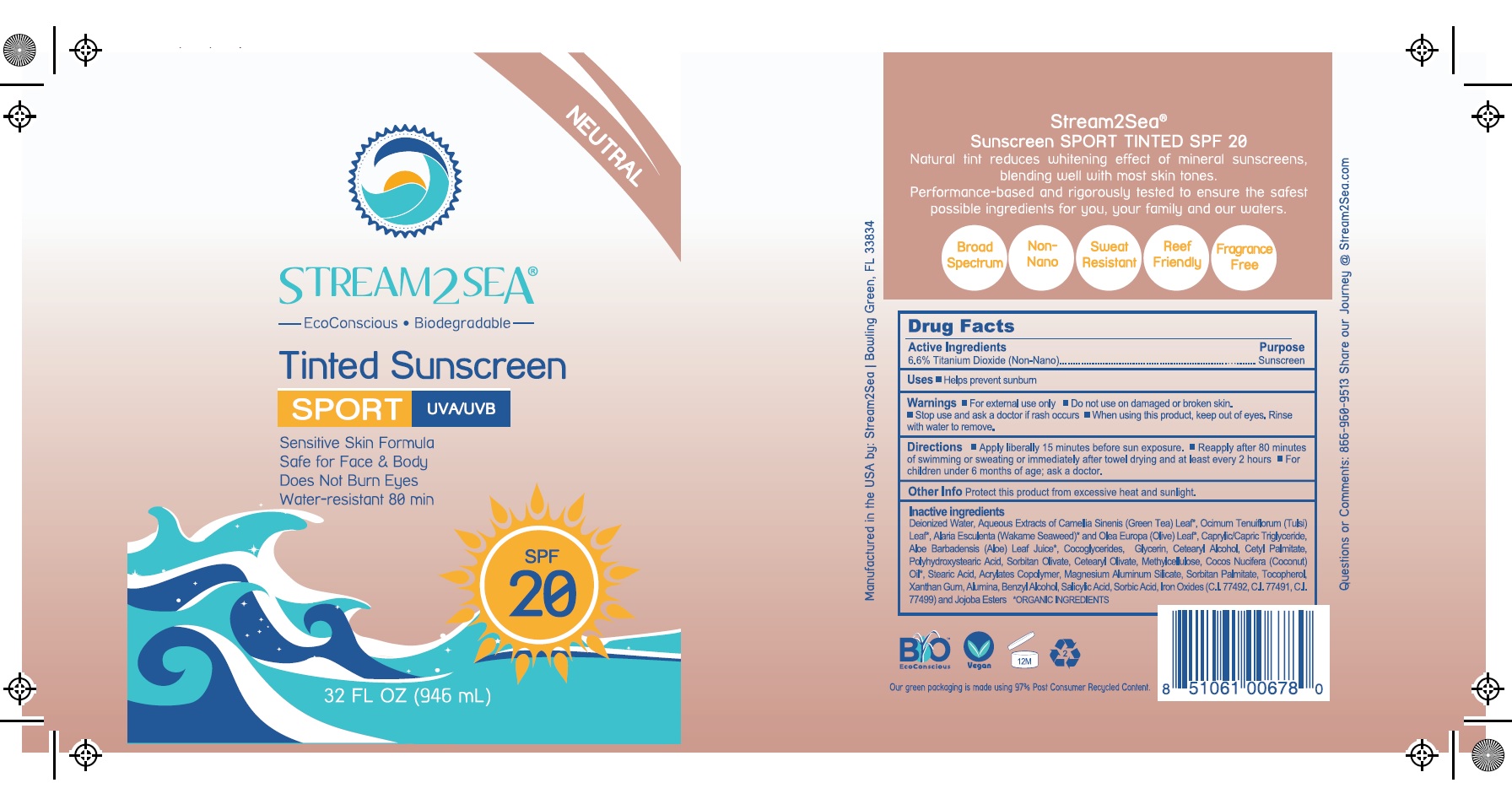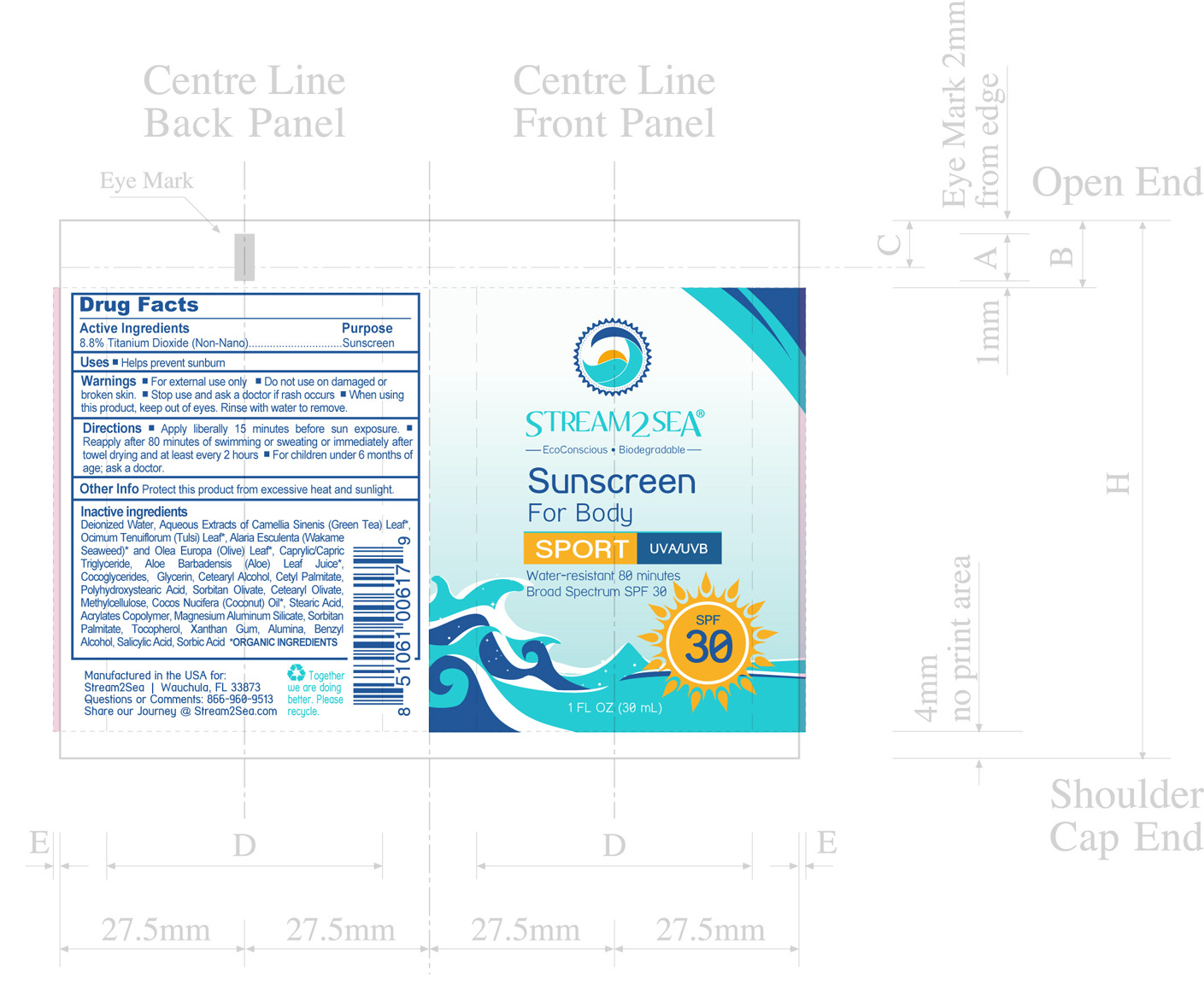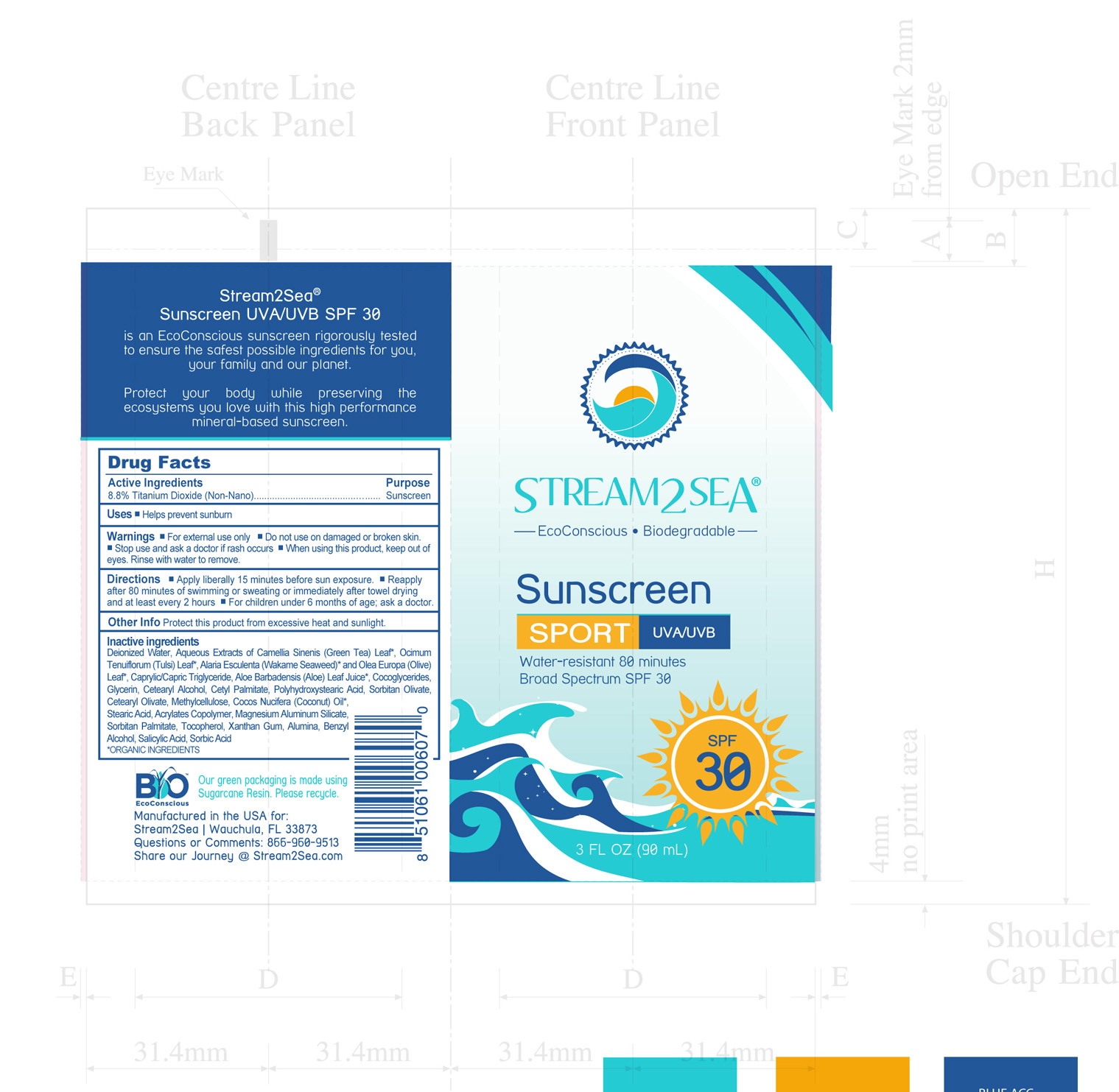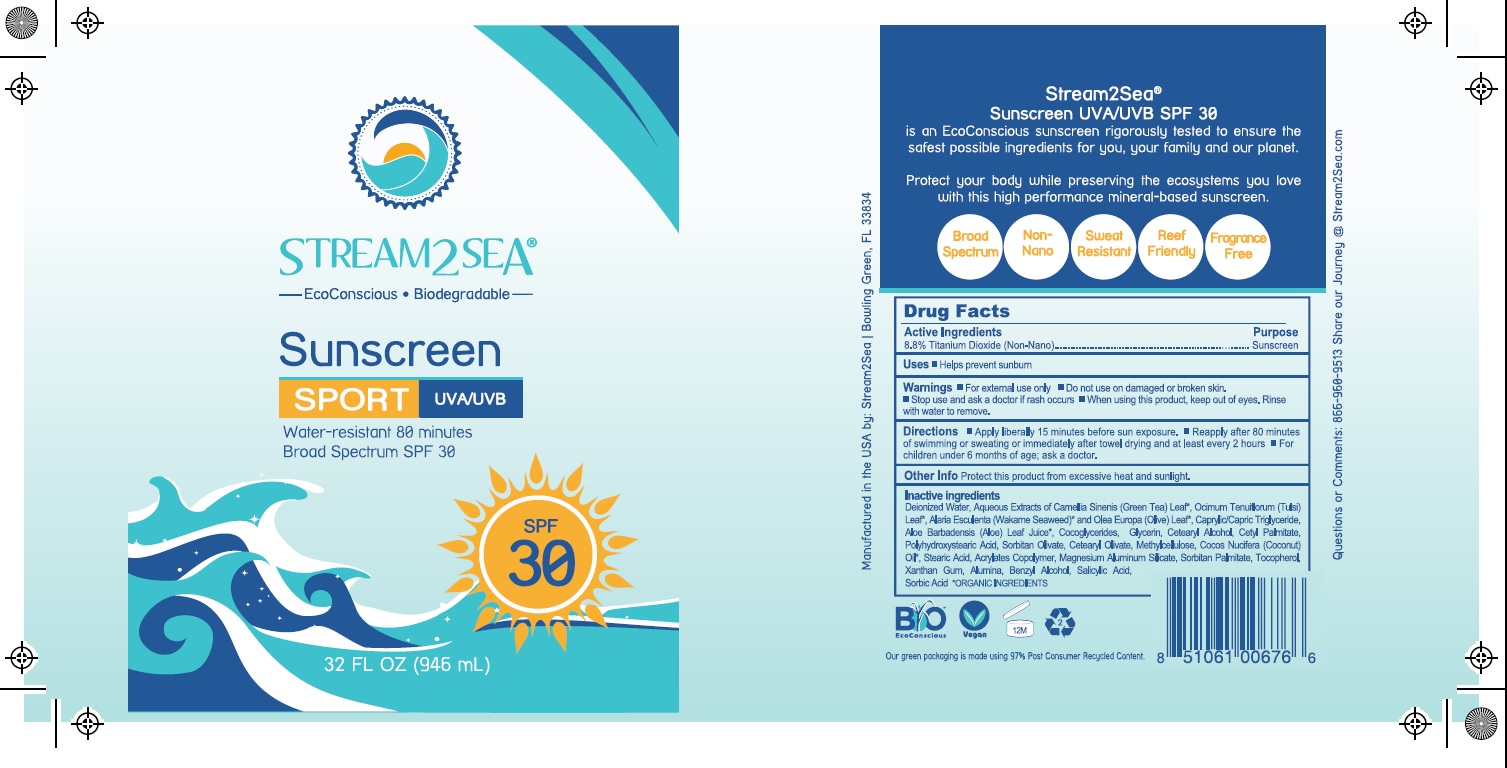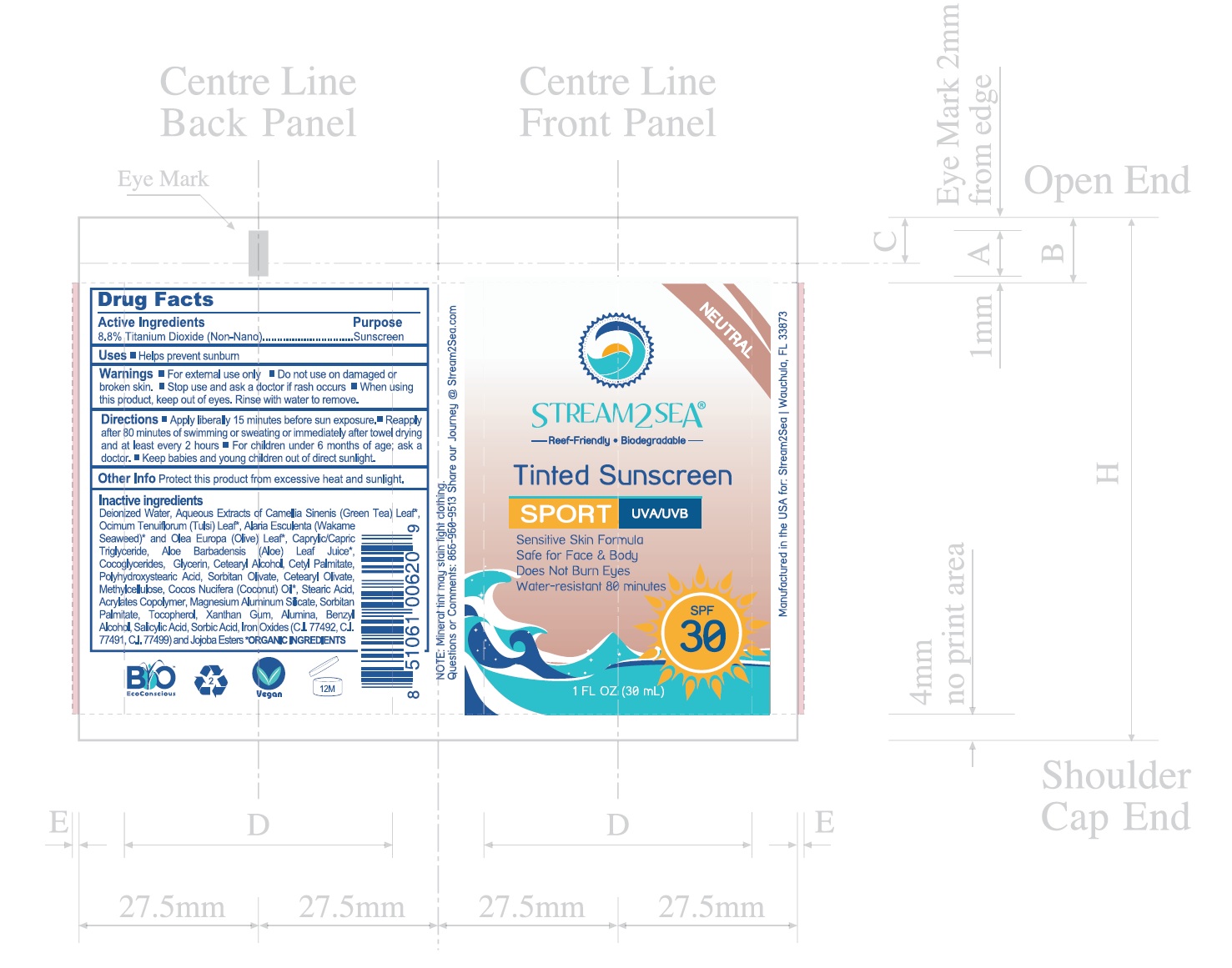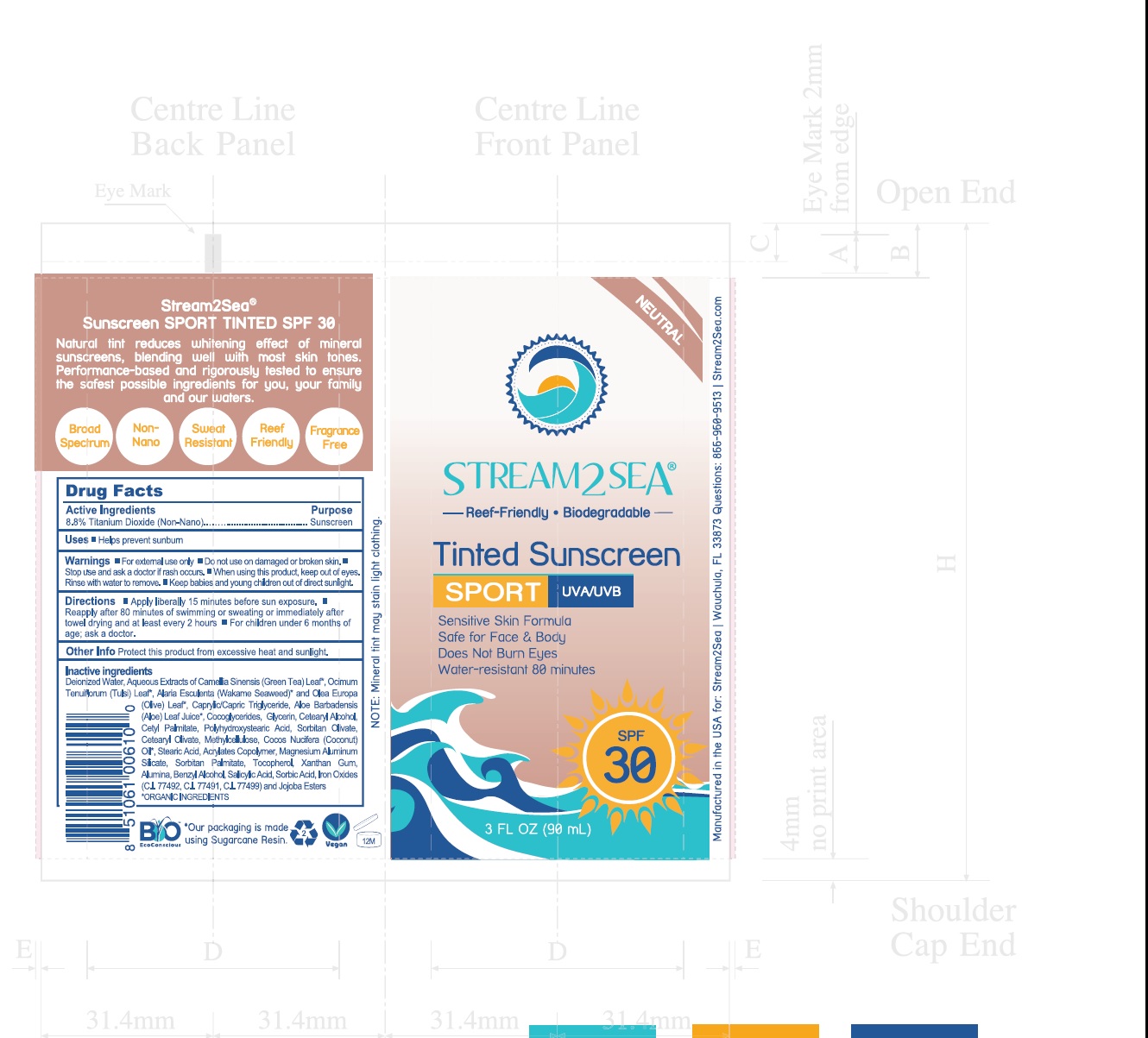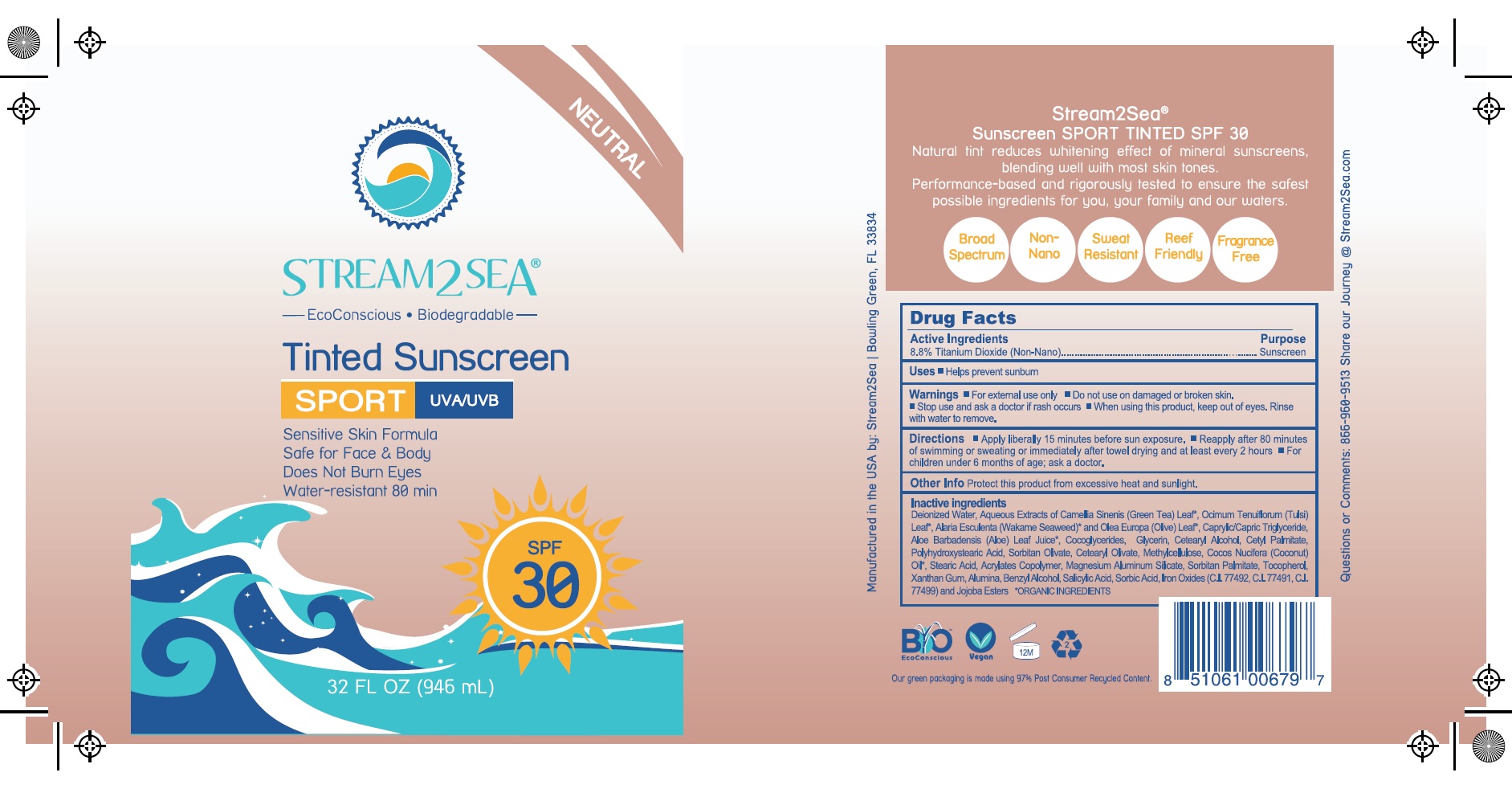 DRUG LABEL: Stream2Sea Broad Spectrum 30
NDC: 69555-030 | Form: LOTION
Manufacturer: Stream2Sea, LLC
Category: otc | Type: HUMAN OTC DRUG LABEL
Date: 20251106

ACTIVE INGREDIENTS: TITANIUM DIOXIDE 1 g/88 mL
INACTIVE INGREDIENTS: GREEN TEA LEAF; HOLY BASIL LEAF; ALARIA ESCULENTA; OLEA EUROPAEA LEAF; WATER; MEDIUM-CHAIN TRIGLYCERIDES; ALOE VERA LEAF; COCO-GLYCERIDES; GLYCERIN; CETOSTEARYL ALCOHOL; CETYL PALMITATE; POLYHYDROXYSTEARIC ACID (2300 MW); SORBITAN OLIVATE; CETEARYL OLIVATE; METHYLCELLULOSE, UNSPECIFIED; COCONUT OIL; STEARIC ACID; LUVISET 360; MAGNESIUM ALUMINUM SILICATE; SORBITAN MONOPALMITATE; TOCOPHEROL; XANTHAN GUM; ALUMINUM OXIDE; BENZYL ALCOHOL; SALICYLIC ACID; SORBIC ACID

Stream2Sea Sport Broad Spectrum

Directions

Apply liberally 15 minutes before sun exposure. Reapply after 80 minutes of swimming or sweating or immediately after towel drying and at least every 2 hours. For children under 6 months of age; ask a doctor.

Warnings

For external use only. Do not use on damaged or broken skin. Stop use and ask a doctor if rash occurs. When using this product, keep out of eyes. RInse with water to remove.

ACTIVE INGREDIENT

Titanium Dioxide 8.8%

INDICATIONS AND USAGE

Helps prevent sunburn.

INACTIVE INGREDIENT

TINTED SPF 30

Deionized Water, Aqueous Extracts of Camellia Sinensis (Green Tea) Leaf*, Ociimum Tenuiflorum (Tulsi) Leaf*, Alara Ssculenta (Wakame Seaweed)* and Olea Europa (Olive) Leaf*, Caprylic Triglyceride, Aloe Barbadensis (Aloe) Leaf Juice*, Cocoglycerides, Glycerin, Cetearyl Alcohol, Cetyl Palmitate, Polyhydroxystearic Acid, Sorbitan Olivate, Cetearyl Olivate, Methylcellulose, Cocos Nucifera (Coconut) Oil*, Stearic Acid, Acrylates Copolymer, Magnesium Aluminum Silicate, Sorbitan Palmitate, Tocopherol, Xanthan Gum, Alumina Benzyl Alcohol, Salicylic Acid, Sorbic Acid, Iron Oxides (CI 77492, CI 77499) and Jojoba Ester

*ORGANIC INGREDIENTS

KEEP OUT OF REACH OF CHILDREN

If product is swallowed, get medical help or contact a Poison Control Center right away.

PURPOSE

Sunscreen.

PACKAGE LABEL.PRINCIPAL DISPLAY PANEL

Stream2Sea Broad Spectrum Sport Face & Body SPF 20 1oz

Stream2Sea Broad Spectrum Sport Face & Body SPF 20 3oz

Stream2Sea Broad Spectrum Sport Face & Body SPF 20 32oz

Stream2Sea Broad Spectrum Sport Face & Body SPF 20-TINTED 1oz

Stream2Sea Broad Spectrum Sport Face & Body SPF 20-TINTED 2oz

Stream2Sea Broad Spectrum Sport Face & Body SPF 20-TINTED 3oz

Stream2Sea Broad Spectrum Sport Face & Body SPF 20-TINTED 32oz

Stream2Sea Broad Spectrum Sport Face & Body SPF 30 1oz

Stream2Sea Broad Spectrum Sport Face & Body SPF 30 3oz

Stream2Sea Water Spot SPF 30 -3 FL OZ (90 ML)

Stream2Sea Broad Spectrum Sport Face & Body SPF 30 32oz

Stream2Sea Broad Spectrum Sport Face & Body SPF 30-TINTED 1oz

Stream2Sea Broad Spectrum Sport Face & Body SPF 30-TINTED 3oz

Stream2Sea Broad Spectrum Sport Face & Body SPF 30-TINTED 32oz

Happy Ocean Water Sport SPF 30 (75 mL)

Happy Ocean Water Sport SPF 30 Tinted (75 mL)